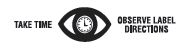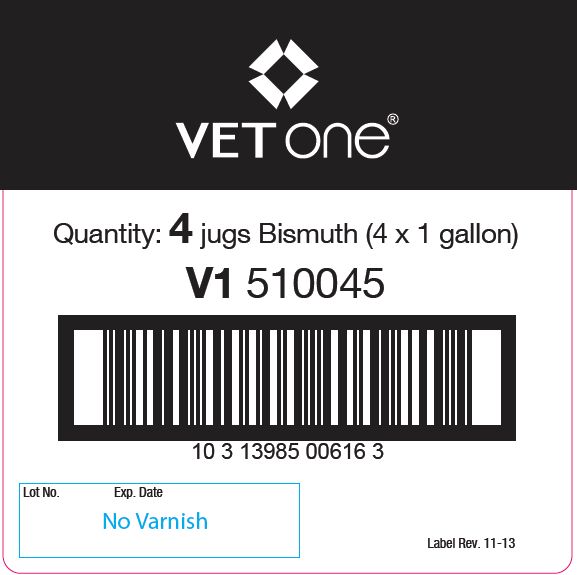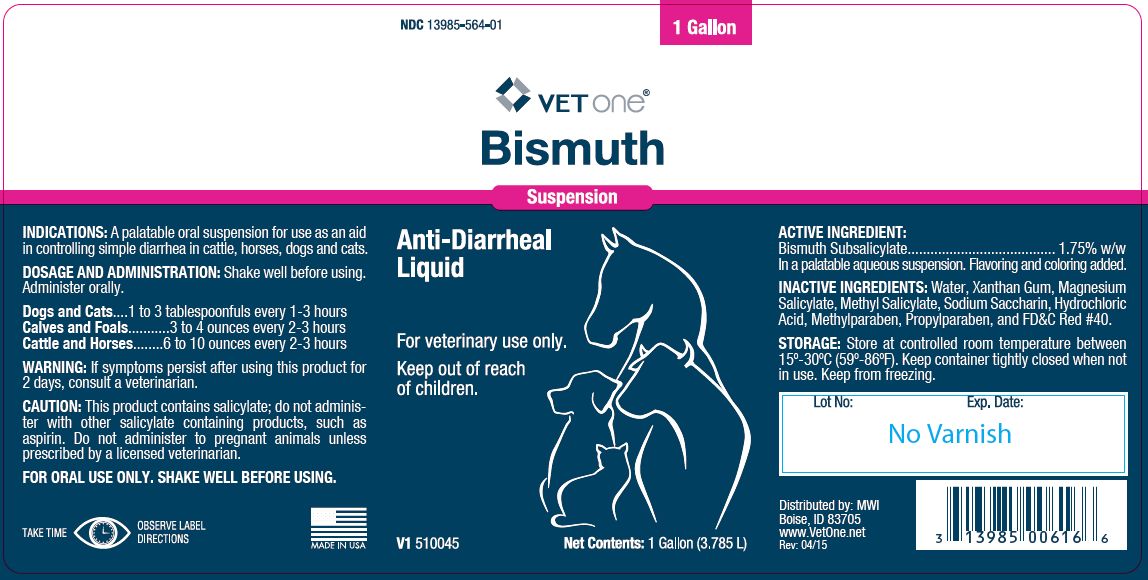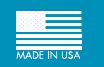 DRUG LABEL: BISMUTH
NDC: 13985-564 | Form: SUSPENSION
Manufacturer: MWI/Vet One
Category: animal | Type: OTC ANIMAL DRUG LABEL
Date: 20221110

ACTIVE INGREDIENTS: BISMUTH SUBSALICYLATE 17.4 g/1 L

Bismuth

PURPOSE

Suspension

Anti-Diarrheal Liquid

KEEP OUT OF REACH OF CHILDREN

For veterinary use only.

Keep out of reach of children.

INDICATIONS

A palatable oral suspension for use as an aid in controlling simple diarrhea in cattle, horses, dogs and cats.

DOSAGE AND ADMINISTRATION:

Shake well before using. Administer orally.

Dogs and Cats....1 to 3 tablespoonfuls every 1-3 hours
Calves and Foals...........3 to 4 ounces every 2-3 hours
Cattle and Horses........6 to 10 ounces every 2-3 hours

WARNING:

If symptoms persist after using this product for 2 days, consult a veterinarian.

CAUTION:

This product contains salicylate; do not administer with other salicylate containing products, such as aspirin. Do not administer to pregnant animals unless prescribed by a licensed veterinarian.

FOR ORAL USE ONLY. SHAKE WELL BEFORE USING.

ACTIVE INGREDIENT:

Bismuth Subsalicylate....................................... 1.75% w/w

In a palatable aqueous suspension. Flavoring and coloring added.

INACTIVE INGREDIENTS:

Water, Xanthan Gum, Magnesium Salicylate, Methyl Salicylate, Sodium Saccharin, Hydrochloric Acid, Methylparaben, Propylparaben, and FD&C Red #40.

STORAGE:

Store at controlled room temperature between 15º-30ºC (59º-86ºF). Keep container tightly closed when not in use. Keep from freezing.

Net Contents:

1 Gallon (3.785 L) V1 510045

INFORMATION FOR OWNERS/CAREGIVERS

Distributed by: MWI
Boise, ID 83705
www.VetOne.net
Rev: 04/15